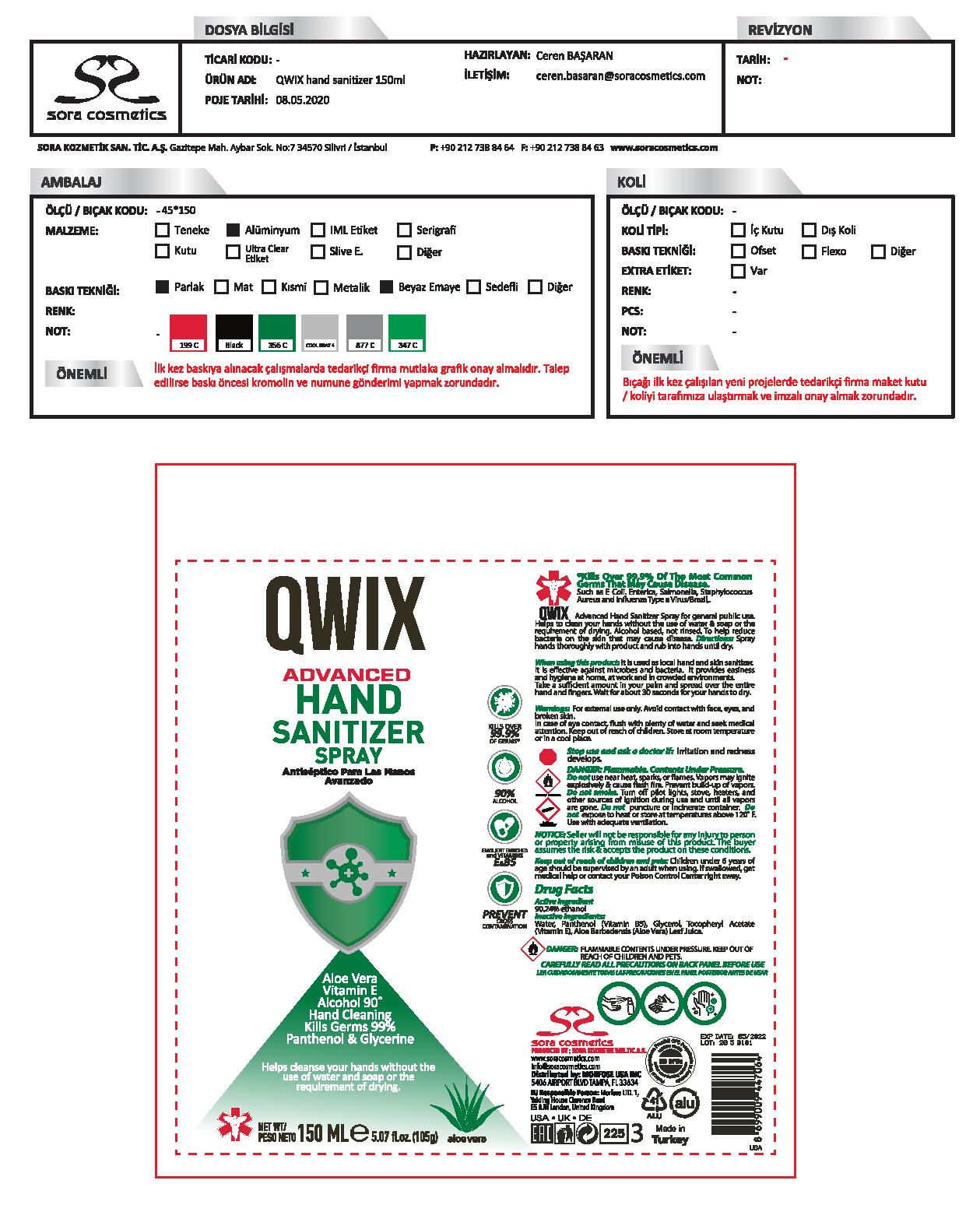 DRUG LABEL: Qwix Hand Sanitizer
NDC: 77462-005 | Form: AEROSOL
Manufacturer: SORA KOZMETIK SANAYI TICARET ANONIM SIRKETI
Category: otc | Type: HUMAN OTC DRUG LABEL
Date: 20200714

ACTIVE INGREDIENTS: ALCOHOL 90.24 mL/100 mL
INACTIVE INGREDIENTS: WATER; PANTHENOL; ALOE VERA LEAF; ALPHA-TOCOPHEROL ACETATE; GLYCERIN

Qwix Hand Sanitizer

Active Ingredient

Ethanol 90.24%

Purpose

Antiseptic

Uses

to help reduce bacteria on the skin that may cause disease.

Warnings

For external use only.
DANGER: Flammable. Contents Under Pressure.
Do not use near heat, sparks, or flames. Vapors may ignite explosively & cause flash fire. Prevent build-up of vapors. Do not smoke. Turn off pilot light, stoves, heaters, and other sources of ignition during use and until all vapors are gone. Do not puncture or incinerate container. Do not expose to heat or store at temperatures about 120F. Use with adequate ventilation.

Stop use and ask a doctor if irritation and redness develops.

WHEN USING

Avoid contact with face, eyes, and broken skin. In case of eye contact, flush with plenty of water and seek medical attention.

Keep out of reach of children and pets: Children under 6 years age should be supervised by an adult when using. If swallowed, get medical help or contact your Poison Control Center right away.

Directions

Spray hands thoroughly with product and rub into hands until dry.

Other Information

Store at room temperature or in a cool place.

Inactive Ingredients

Water, Panthenol (Vitamin B5), Glycerol, Tocopheryl Acetate (Vitamin E), Aloe Barbadensis (Aloe Vera) Leaf Juice.